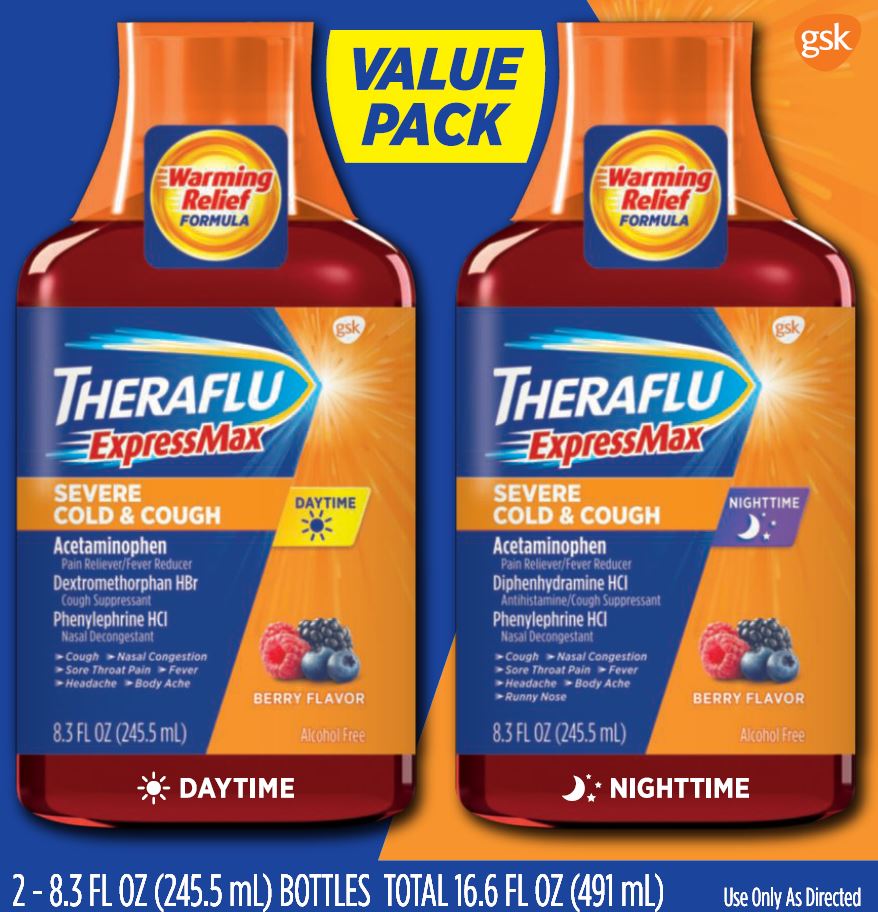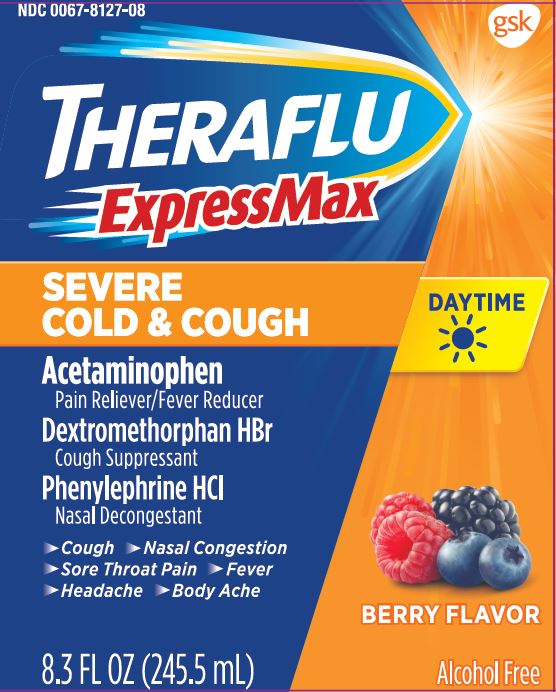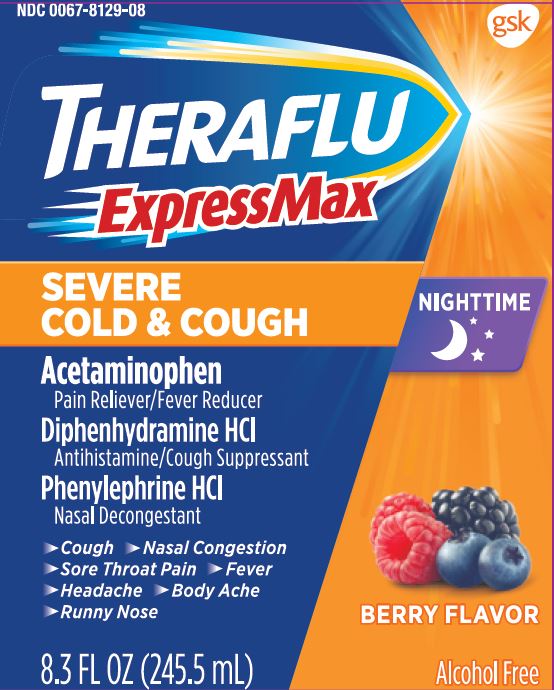 DRUG LABEL: Theraflu ExpressMax

NDC: 0067-8125 | Form: KIT | Route: ORAL
Manufacturer: Haleon US Holdings LLC
Category: otc | Type: HUMAN OTC DRUG LABEL
Date: 20240410

ACTIVE INGREDIENTS: ACETAMINOPHEN 650 mg/30 mL; DEXTROMETHORPHAN HYDROBROMIDE 20 mg/30 mL; PHENYLEPHRINE HYDROCHLORIDE 10 mg/30 mL; ACETAMINOPHEN 650 mg/30 mL; DIPHENHYDRAMINE HYDROCHLORIDE 25 mg/30 mL; PHENYLEPHRINE HYDROCHLORIDE 10 mg/30 mL
INACTIVE INGREDIENTS: ACESULFAME POTASSIUM; ANHYDROUS CITRIC ACID; EDETATE DISODIUM; FD&C BLUE NO. 1; FD&C RED NO. 40; GLYCERIN; MALTITOL; PROPYLENE GLYCOL; SODIUM BENZOATE; SODIUM CITRATE, UNSPECIFIED FORM; WATER; ACESULFAME POTASSIUM; ANHYDROUS CITRIC ACID; EDETATE DISODIUM; FD&C BLUE NO. 1; FD&C RED NO. 40; GLYCERIN; MALTITOL; PROPYLENE GLYCOL; SODIUM BENZOATE; SODIUM CITRATE, UNSPECIFIED FORM; WATER

Drug Facts

Active ingredients (in each 30 mL)

Acetaminophen 650 mg

Dextromethorphan HBr 20 mg

Phenylephrine HCl 10 mg

Purposes

Pain reliever/fever reducer

Cough suppressant

Nasal decongestant

Uses

- temporarily relieves these symptoms due to a cold:
  - minor aches and pains
  - minor sore throat pain
  - headache
  - nasal and sinus congestion
  - cough due to minor throat and bronchial irritation
- temporarily reduces fever

Warnings

Liver warning:This product contains acetaminophen. Severe liver damage may occur if you take

- more than 4,000 mg of acetaminophen in 24 hours
- with other drugs containing acetaminophen
- 3 or more alcoholic drinks every day while using this product

Allergy alert:Acetaminophen may cause severe skin reactions. Symptoms may include:

- skin reddening
- blisters
- rash
- If a skin reaction occurs, stop use and seek medical help right away.

Sore throat warning:If sore throat is severe, persists for more than 2 days, is accompanied or followed by fever, headache, rash, nausea, or vomiting consult a doctor promptly.

Do Not Use

- in a child under 12 years of age
- if you are allergic to acetaminophen
- with any other drug containing acetaminophen (prescription or nonprescription). If you are not sure whether a drug contains acetaminophen, ask a doctor or pharmacist.
- if you are now taking a prescription monoamine oxidase inhibitor (MAOI) (certain drugs for depression, psychiatric, or emotional conditions, or Parkinson’s disease), or for 2 weeks after stopping the MAOI drug. If you do not know if your prescription drug contains an MAOI, ask a doctor or pharmacist before taking this product.

Ask a doctor before use if you have

- liver disease
- heart disease
- high blood pressure
- thyroid disease
- diabetes
- trouble urinating due to an enlarged prostate gland
- cough that occurs with too much phlegm (mucus)
- cough that lasts or is chronic such as occurs with smoking, asthma or emphysema

Ask a doctor or pharmacist before use if you are

- taking the blood thinning drug warfarin

When using this product

- do not exceed recommended dosage

Stop use and ask a doctor if

- nervousness, dizziness, or sleeplessness occurs
- fever gets worse or lasts more than 3 days
- redness or swelling is present
- new symptoms occur
- pain, cough or nasal congestion gets worse or lasts more than 7 days
- cough comes back or occurs with rash or headache that lasts. These could be signs of a serious condition.

If pregnant or breast-feeding,

ask a health professional before use.

Keep out of reach of children.

In case of overdose, get medical help or contact a Poison Control Center right away. Prompt medical attention is critical for adults as well as for children even if you do not notice any signs or symptoms.

Directions

- do not use more than directed
- measure the dose correctly using the enclosed dosing cup
- take every 4 hours in dosing cup provided, while symptoms persist
- do not take more than 5 doses (150 mL) in 24 hours unless directed by a doctor

1. Age

1. Dose

1. adults and children 12 years of age and over

1. 30 mL

1. children under 12 years of age

1. do not use

Other information

- each 30 mL contains: potassium 35 mg, sodium 17 mg
- store at controlled room temperature 20-25°C (68-77°F)

Inactive ingredients

acesulfame potassium, anhydrous citric acid, edetate disodium, FD&C blue no. 1, FD&C red no. 40, flavors, glycerin, maltitol solution, propylene glycol, purified water, sodium benzoate, sodium citrate

Questions?

call 1-800-328-5259

Active ingredients (in each 30 mL)

Acetaminophen 650 mg

Diphenhydramine HCl 25 mg

Phenylephrine HCl 10 mg

Purposes

Pain Reliever/fever reducer

Antihistamine/cough suppressant

Nasal decongestant

Uses

- temporarily relieves these symptoms due to a cold:
  - minor aches and pains
  - minor sore throat pain
  - headache
  - nasal and sinus congestion
  - runny nose
  - sneezing
  - itchy nose or throat
  - itchy, watery eyes due to hay fever
  - cough due to minor throat and bronchial irritation
- temporarily reduces fever

Warnings

Liver warning:This product contains acetaminophen. Severe liver damage may occur if you take

- more than 4,000 mg of acetaminophen in 24 hours
- with other drugs containing acetaminophen
- 3 or more alcoholic drinks every day while using this product

Allergy alert:Acetaminophen may cause severe skin reactions. Symptoms may include:

- skin reddening
- blisters
- rash

If a skin reaction occurs, stop use and seek medical help right away.

Sore throat warning:If sore throat is severe, persists for more than 2 days, is accompanied or followed by fever, headache, rash, nausea, or vomiting consult a doctor promptly.

Do not use

- in a child under 12 years of age
- if you are allergic to acetaminophen
- with any other drug containing acetaminophen (prescription or nonprescription). If you are not sure whether a drug contains acetaminophen, ask a doctor or pharmacist.
- with any other product containing diphenhydramine, even one used on the skin
- if you are now taking a prescription monoamine oxidase inhibitor (MAOI) (certain drugs for depression, psychiatric, or emotional conditions, or Parkinson’s disease), or for 2 weeks after stopping the MAOI drug. If you do not know if your prescription drug contains a MAO, ask a doctor or pharmacist before taking this product.

Ask a doctor before use if you have

- liver disease
- heart disease
- high blood pressure
- thyroid disease
- diabetes
- glaucoma
- trouble urinating due to an enlarged prostate gland
- a breathing problem such as emphysema or chronic bronchitis
- cough that occurs with too much phlegm (mucus)
- cough that lasts or is chronic such as occurs with smoking, asthma, or emphysema

Ask a doctor or pharmacist before use if you are

- taking sedatives or tranquilizers
- taking the blood thinning drug warfarin

When using this product

- do not exceed recommended dosage
- avoid alcoholic drinks
- marked drowsiness may occur
- alcohol, sedatives, and tranquilizers may increase drowsiness
- be careful when driving a motor vehicle or operating machinery
- excitability may occur, especially in children

Stop use and ask a doctor if

- nervousness, dizziness, or sleeplessness occurs
- fever gets worse or lasts more than 3 days
- redness or swelling is present
- new symptoms occur
- pain, cough or nasal congestion gets worse or lasts more than 7 days
- cough comes back or occurs with rash or headache that lasts. These could be signs of a serious condition.

If pregnant or breast-feeding,

ask a health professional before use.

Keep out of reach of children.

In case of overdose, get medical help or contact a Poison Control Center right away. Prompt medical attention is critical for adults as well as for children even if you do not notice any signs or symptoms.

Directions

- do not use more than directed
- measure the dose correctly using the enclosed dosing cup
- take every 4 hours in dosing cup provided, while symptoms persist.
- do not take more than 5 doses (150 mL) in 24 hours unless directed by a doctor

1. Age

1. Dose

1. adults and children 12 years of age and over

1. 30 mL

1. children under 12 years of age

1. Do not use

Other information

- each 30 mL contains: potassium 35 mg, sodium 17 mg
- store at controlled room temperature 20-25°C (68-77°F)

Inactive ingredients

acesulfame potassium, anhydrous citric acid, edetate disodium, FD&C blue no. 1, FD&C red no. 40, flavors, glycerin, maltitol solution, propylene glycol, purified water, sodium benzoate, sodium citrate

Questions?

call 1-800-328-5259

Other Safety Information

DO NOT TAKE BOTH PRODUCTS AT THE SAME TIME OR TAKE MORE THAN 5 DOSES IN TOTAL IN ANY 24 HOUR PERIOD.

DO NOT TAKE A DOSE OF THE NIGHTTIME PRODUCT SOONER THAN 4 HOURS AFTER THE LAST DOSE OF THE DAYTIME PRODUCT UNLESS DIRECTED BY YOUR DOCTOR.

PARENTS:Learn about teen medicine abuse

www.StopMedicineAbuse.org

TAMPER-EVIDENT INNER UNIT. DO NOT USE IF NECKBAND PRINTED WITH “SEALED FOR SAFETY” IS TORN OR MISSING

Distributed by: GSK Consumer Healthcare

Warren, NJ 07059

©2019 GSK group of companies or its licensor.

13440

Principal Display Panel

NDC 0067-8125-16

THERAFLU

ExpressMax

DAYTIME

SEVERE COLD & COUGH

BERRY FLAVOR

ACETAMINOPHEN

PAIN RELIEVER/FEVER REDUCER

DEXTROMETHORPHAN HBr

COUGH SUPPRESSANT

PHENYLEPHRINE HCl

NASAL DECONGESTANT

• Cough • Nasal Congestion

• Sore Throat Pain • Fever

• Headache • Body Ache

8.3 FL OZ (245.5mL)

Alcohol Free

DAYTIME

THERAFLU

ExpressMax

NIGHTTIME

SEVERE COLD & COUGH

BERRY FLAVOR

ACETAMINOPHEN

PAIN RELIEVER/FEVER REDUCER

DIPHENHYDRAMINE HCl

ANTIHISTAMINE/COUGH SUPPRESSANT

PHENYLEPHRINE HCl

NASAL DECONGESTANT

• Cough • Nasal Congestion

• Sore Throat Pain • Fever

• Headache • Body Ache

• Runny Nose

8.3 FL OZ (245.5mL)

Alcohol Free

NIGHTTIME

- 2 – 8.3 FL OZ (245.5 mL) BOTTLES TOTAL 16.6 FL OZ (491 mL)Use Only As Directed

Principal Display Panel

NDC 0067-8127-08

THERAFLU

ExpressMax

DAYTIME

SEVERE COLD & COUGH

BERRY FLAVOR

ACETAMINOPHEN

PAIN RELIEVER/FEVER REDUCER

DEXTROMETHORPHAN HBr

COUGH SUPPRESSANT

PHENYLEPHRINE HCl

NASAL DECONGESTANT

• Cough • Nasal Congestion

• Sore Throat Pain • Fever

• Headache • Body Ache

8.3 FL OZ (245.5mL)

Alcohol Free

Principal Display Panel

NDC 0067-8129-08

THERAFLU

ExpressMax

NIGHTTIME

SEVERE COLD & COUGH

BERRY FLAVOR

ACETAMINOPHEN

PAIN RELIEVER/FEVER REDUCER

DIPHENHYDRAMINE HCl

ANTIHISTAMINE/COUGH SUPPRESSANT

PHENYLEPHRINE HCl

NASAL DECONGESTANT

• Cough • Nasal Congestion

• Sore Throat Pain • Fever

• Headache • Body Ache

• Runny Nose

8.3 FL OZ (245.5mL)

Alcohol Free